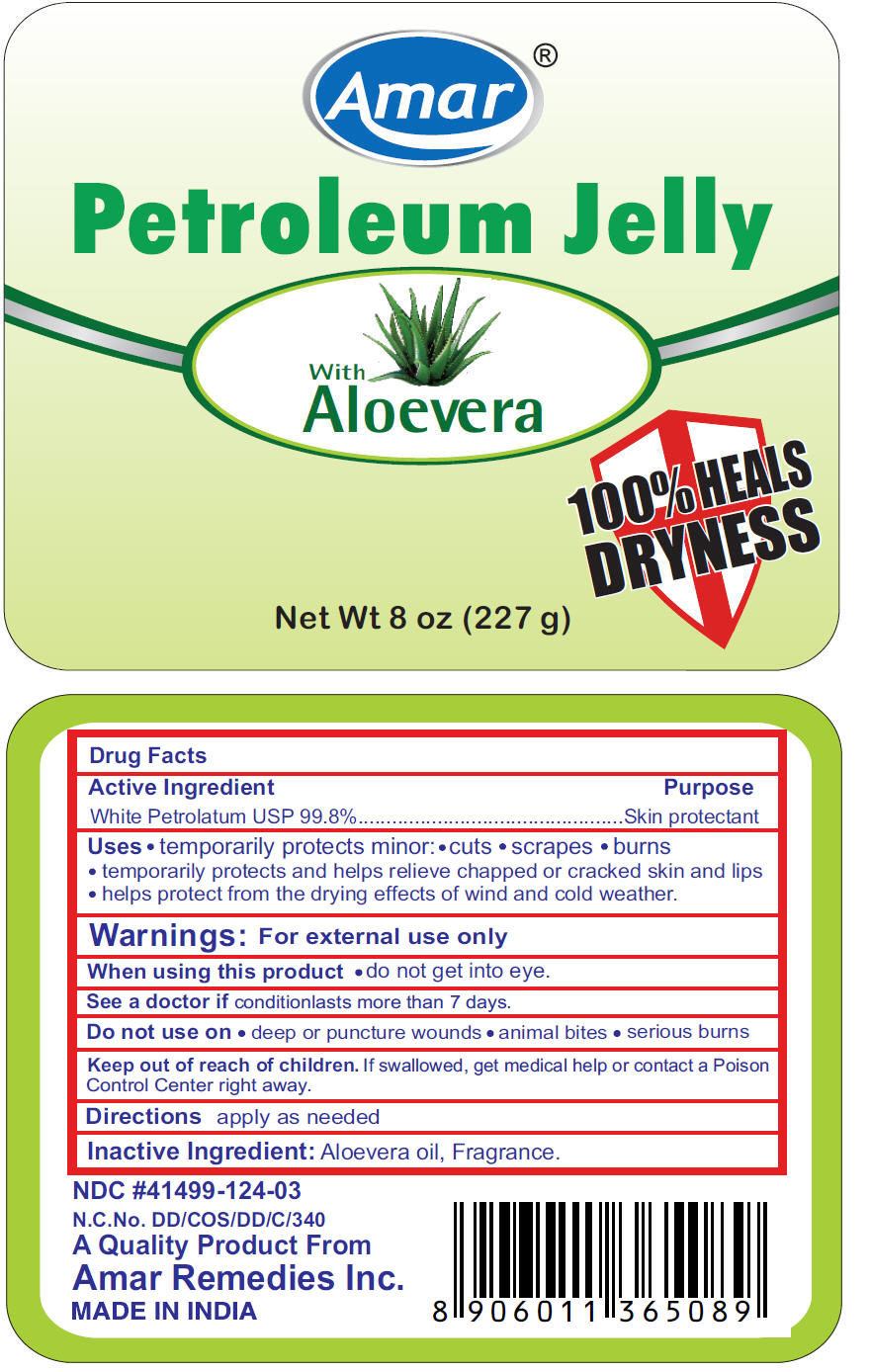 DRUG LABEL: Amar Petroleum 
NDC: 41499-124 | Form: JELLY
Manufacturer: Amar Remedies Limited
Category: otc | Type: HUMAN OTC DRUG LABEL
Date: 20110727

ACTIVE INGREDIENTS: Petrolatum 99.8 g/100 g
INACTIVE INGREDIENTS: Aloe Vera Leaf 0.01 g/100 g

Amar ®
Petroleum Jelly

Drug Facts

Active Ingredient

White Petrolatum USP 99.8%

Purpose

Skin protectant

Uses

- temporarily protects minor:
  - cuts
  - scrapes
  - burns
- temporarily protects and helps relieve chapped or cracked skin and lips
- helps protect from the drying effects of wind and cold weather.

Warnings

For external use only

When using this product

- do not get into eye.

ASK DOCTOR

See a doctor if conditionlasts more than 7 days

Do not use on

- deep or puncture wounds
- animal bites
- serious burns

Keep out of reach of children. If swallowed, get medical help or contact a Poison Control Center right away.

Directions

apply as needed

Inactive Ingredient

Aloevera oil, Fragrance.

PRINCIPAL DISPLAY PANEL - 227 g Jar

Amar ®

Petroleum Jelly

With
Aloevera

100% HEALS
DRYNESS

Net Wt 8 oz (227 g)